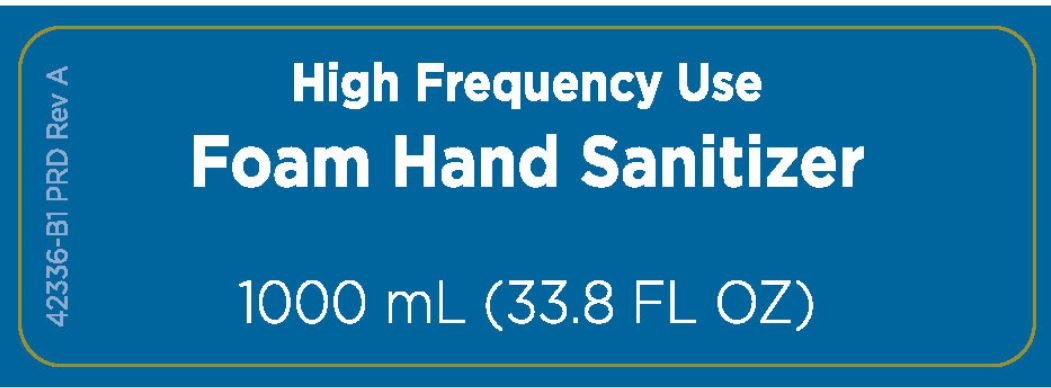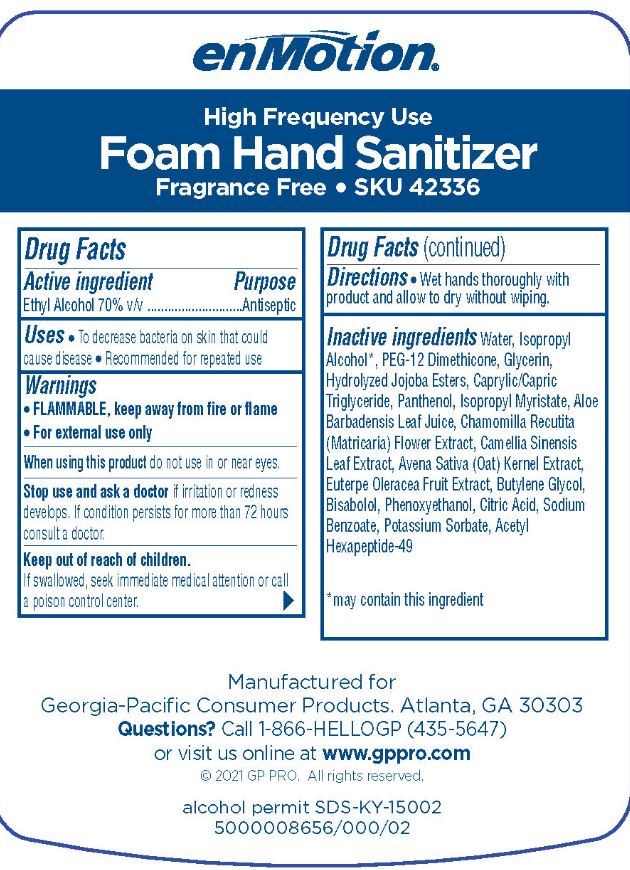 DRUG LABEL: enMotion Foam

NDC: 54622-121 | Form: SOLUTION
Manufacturer: Georgia-Pacific Consumer Products LP
Category: otc | Type: HUMAN OTC DRUG LABEL
Date: 20250123

ACTIVE INGREDIENTS: ALCOHOL 0.7 mL/1 mL
INACTIVE INGREDIENTS: WATER; ISOPROPYL ALCOHOL; PEG-12 DIMETHICONE; GLYCERIN; HYDROLYZED JOJOBA ESTERS (ACID FORM); GLYCERYL CAPRYLATE/CAPRATE; PANTHENOL; ISOPROPYL MYRISTATE; ALOE VERA LEAF; MATRICARIA CHAMOMILLA FLOWERING TOP OIL; CAMELLIA SINENSIS FLOWER; AVENA SATIVA WHOLE; EUTERPE OLERACEA WHOLE; BUTYLENE GLYCOL; .BETA.-BISABOLOL; PHENOXYETHANOL; CITRIC ACID MONOHYDRATE; SODIUM BENZOATE; POTASSIUM SORBATE; ACETYL HEXAPEPTIDE-49

enMotion High Frequency Foam Hand Sanitizer Fragrance Free 54622-121

Active ingredient

Ethyl Alcohol 70% v/v

Purpose

Antiseptic

Uses

- To decrease bacteria on skin that could cause disease
- Recommended for repeated use

Warnings

- FLAMMABLE, keep away from fire or flame
- For external use only

When using this product do not use in or near eyes.

Stop use and ask a doctor if irritation or redness develops. If condition persists for more than 72 hours consult a doctor.

Keep out of reach of children.

If swallowed, seek immediate medical attention or call a poison control center.

Directions

- Wet hands thoroughly with product and allow to dry without wiping.

Inactive ingredients

Water, Isopropyl Alcohol*, PEG-12 Dimethicone, Glycerin, Hydrolyzed Jojoba Esters, Caprylic/Capric Triglyceride, Panthenol, Isopropyl Myristate, Aloe Barbadensis Leaf Juice, Chamomilla Recutita (Matricaria) Flower Extract, Camellia Sinensis Leaf Extract, Avena Sativa (Oat) Kernel Extract, Euterpe Oleracea Fruit Extract, Butylene Glycol, Bisabolol, Phenoxyethanol, Citric Acid, Sodium Benzoate, Potassium Sorbate, Acetyl Hexapeptide-49

*may contain this ingredient

Rear label text

enMotion

High Frequency Use

Foam Hand Sanitizer

Fragrance Free SKU 42336

Manufactured for

Georgia-Pacific Consumer Products. Atlanta, GA 30303

Quesitons?Call 1-866-HELLOGP (435-5647)

or visit us online at www.gppro.com

(c) 2021 GP PRO. All rights reserved.

alcohol permit SDS-KY-15002

5000008656/000/02

principal display panel

High Frequency Use

Foam Hand Sanitizer

1000 mL (33.8 FL OZ)